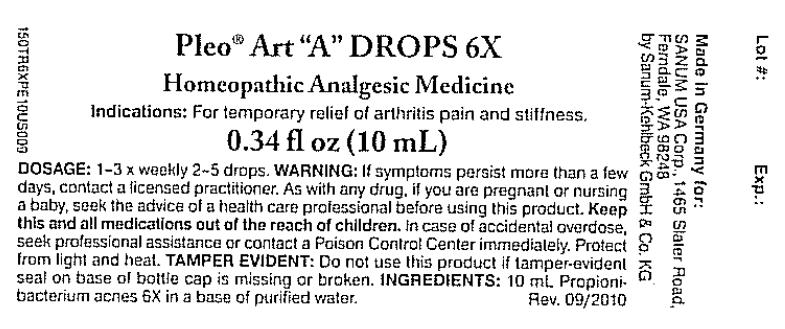 DRUG LABEL: Pleo Art A
NDC: 60681-0301 | Form: SOLUTION/ DROPS
Manufacturer: Sanum Kehlbeck GmbH & Co. KG
Category: homeopathic | Type: HUMAN OTC DRUG LABEL
Date: 20110801

ACTIVE INGREDIENTS: propionibacterium acnes 6 [hp_X]/10 mL
INACTIVE INGREDIENTS: water

Pleo® Art
"A"
DROPS 6X

PURPOSE

Homeopathic Analgesic Medicine

0.34 fl oz
(10 mL)

Indications

For temporary relief of arthritis pain and stiffness.

INGREDIENTS

INACTIVE INGREDIENT

10 mL Propionibacterium acnes 6X in a base of purified water.

Tamper Evident

Use this product only if tamper-evident strip on base of bottle cap is intact.

DOSAGE

1–3 x weekly 2–5 drops.

WARNING

If symptoms persist more than a few days, contact a licensed practitioner. As with any drug, if you are pregnant or nursing a baby, seek the advice of a health care professional before using this product.

KEEP OUT OF REACH OF CHILDREN

Keep this and all medications out of the reach of children. In case of accidental overdose, seek professional assistance or contact a Poison Control Center immediately.

STORAGE AND HANDLING

Protect from light and heat.

Made in Germany

Distributed by:
SANUM USA Corp.
1465 Slater Road
Ferndale, WA 98248

Manufactured By:
Sanum-Kehlbeck,
GmbH & Co. KG

Rev. 03/2005

PRINCIPAL DISPLAY PANEL - 10 mL Label

Pleo® Art "A" DROPS 6X

Homeopathic Analgesic Medicine

Indications: For temporary relief of arthritis pain and stiffness.

0.34 fl oz (10 mL)

DOSAGE: 1–3 x weekly 2–5 drops. WARNING: If symptoms persist more than a few
days, contact a licensed practitioner. As with any drug, if you are pregnant or nursing
a baby, seek the advice of a health care professional before using this product. Keep
this and all medications out of the reach of children. In case of accidental overdose,
seek professional assistance or contact a Poison Control Center immediately. Protect
from light and heat. TAMPER EVIDENT: Do not use this product if tamper-evident
seal on base of bottle cap is missing or broken. INGREDIENTS: 10 mL Propioni-
bacterium acnes 6X in a base of purified water.
Rev. 09/2010